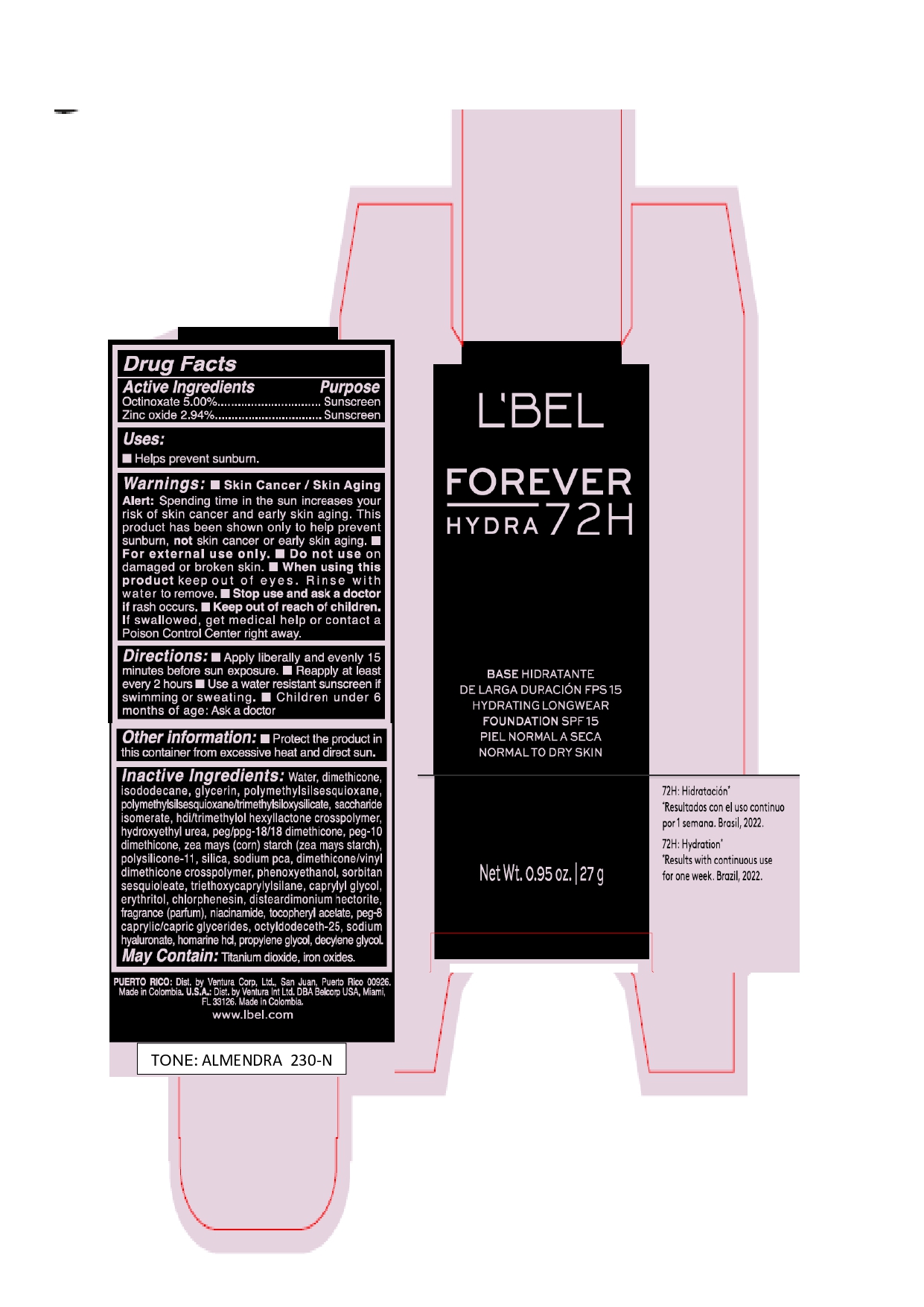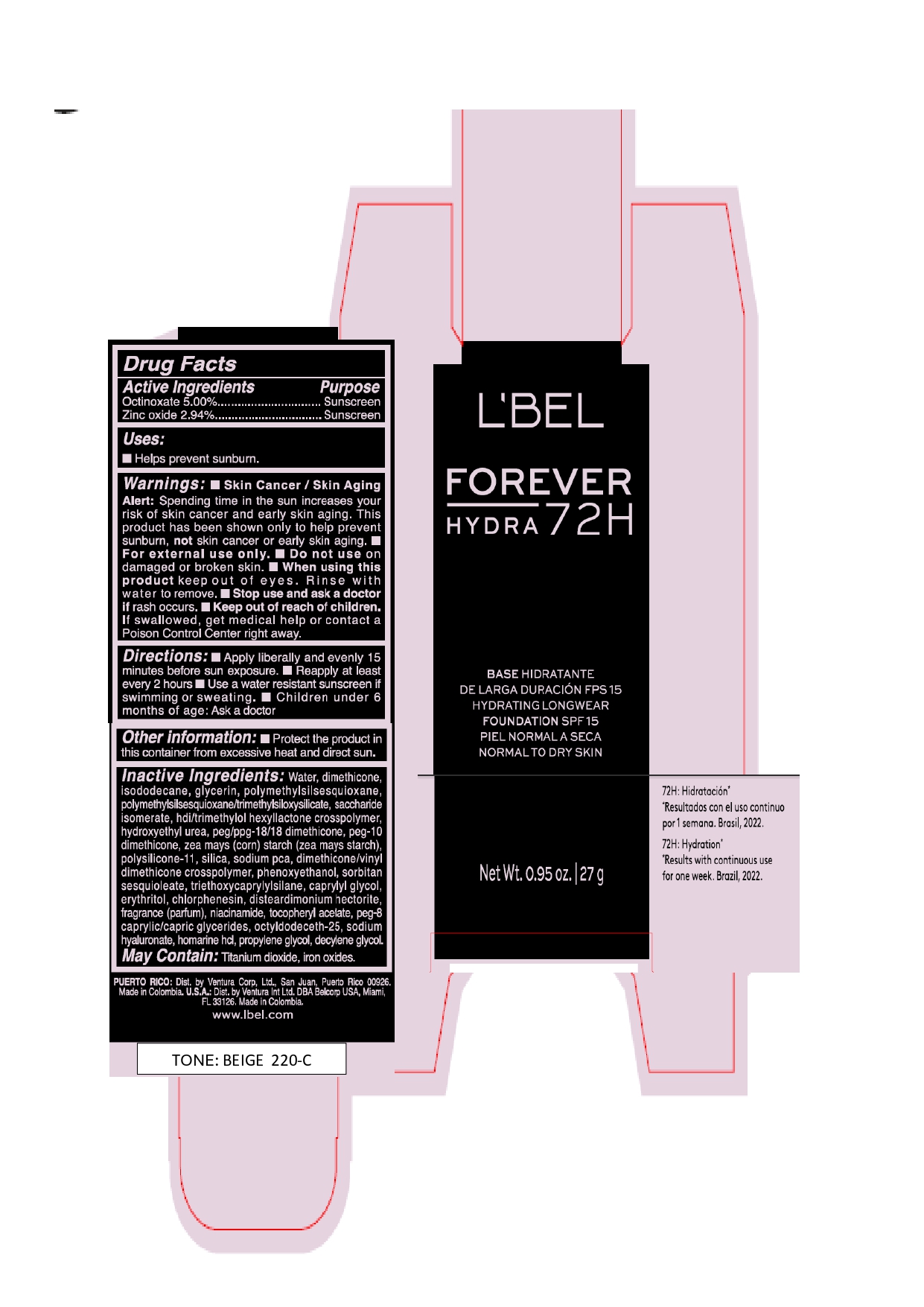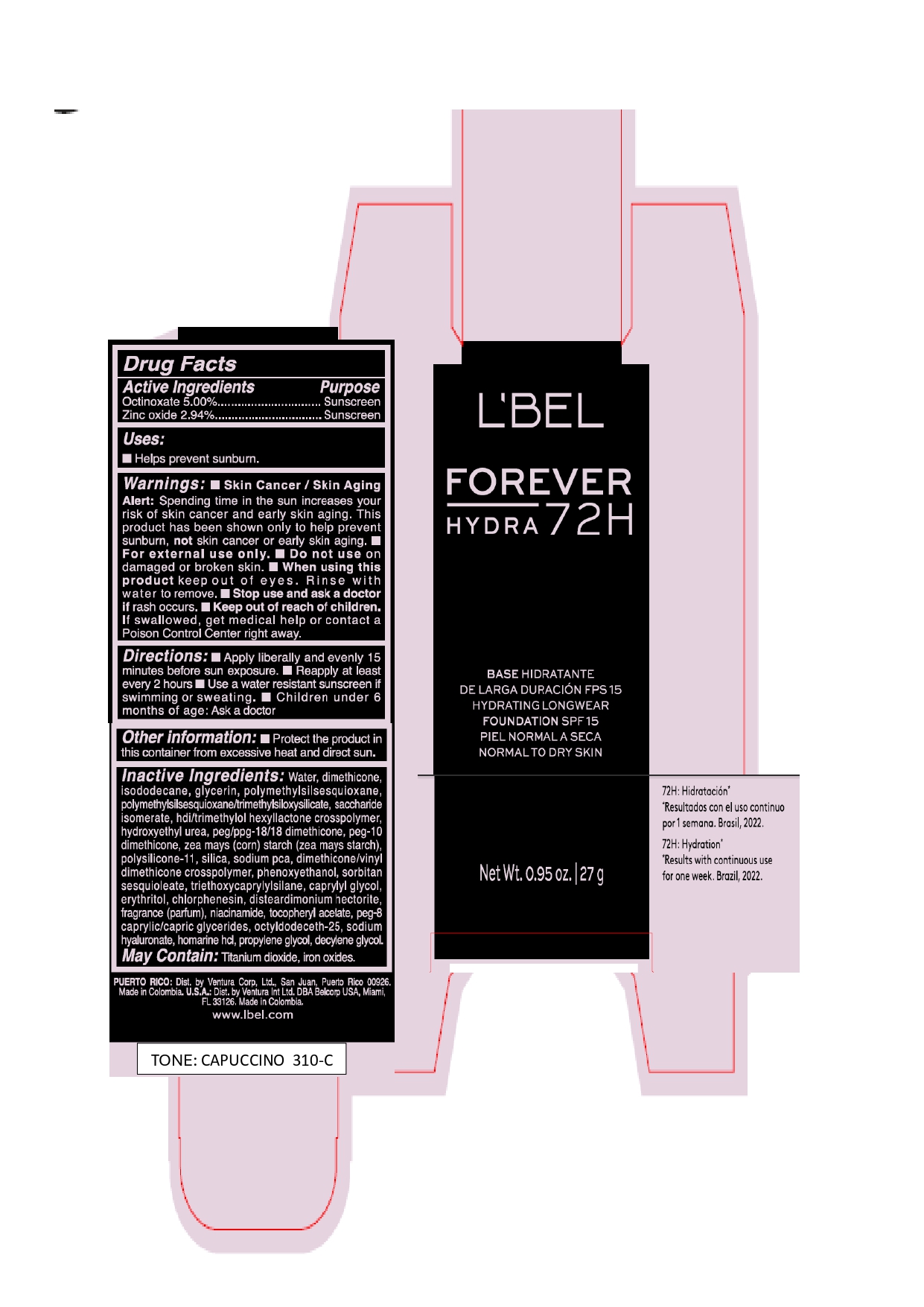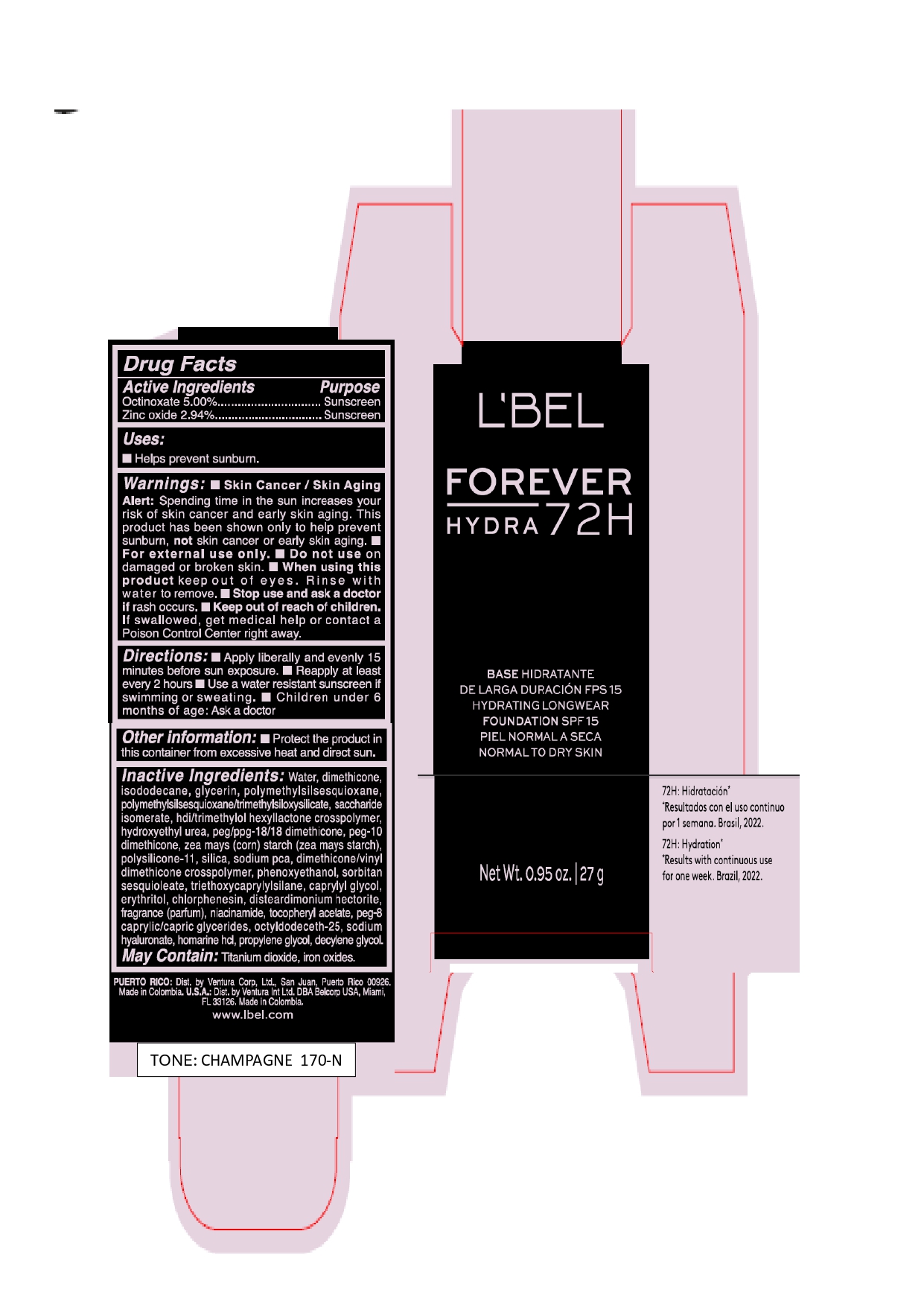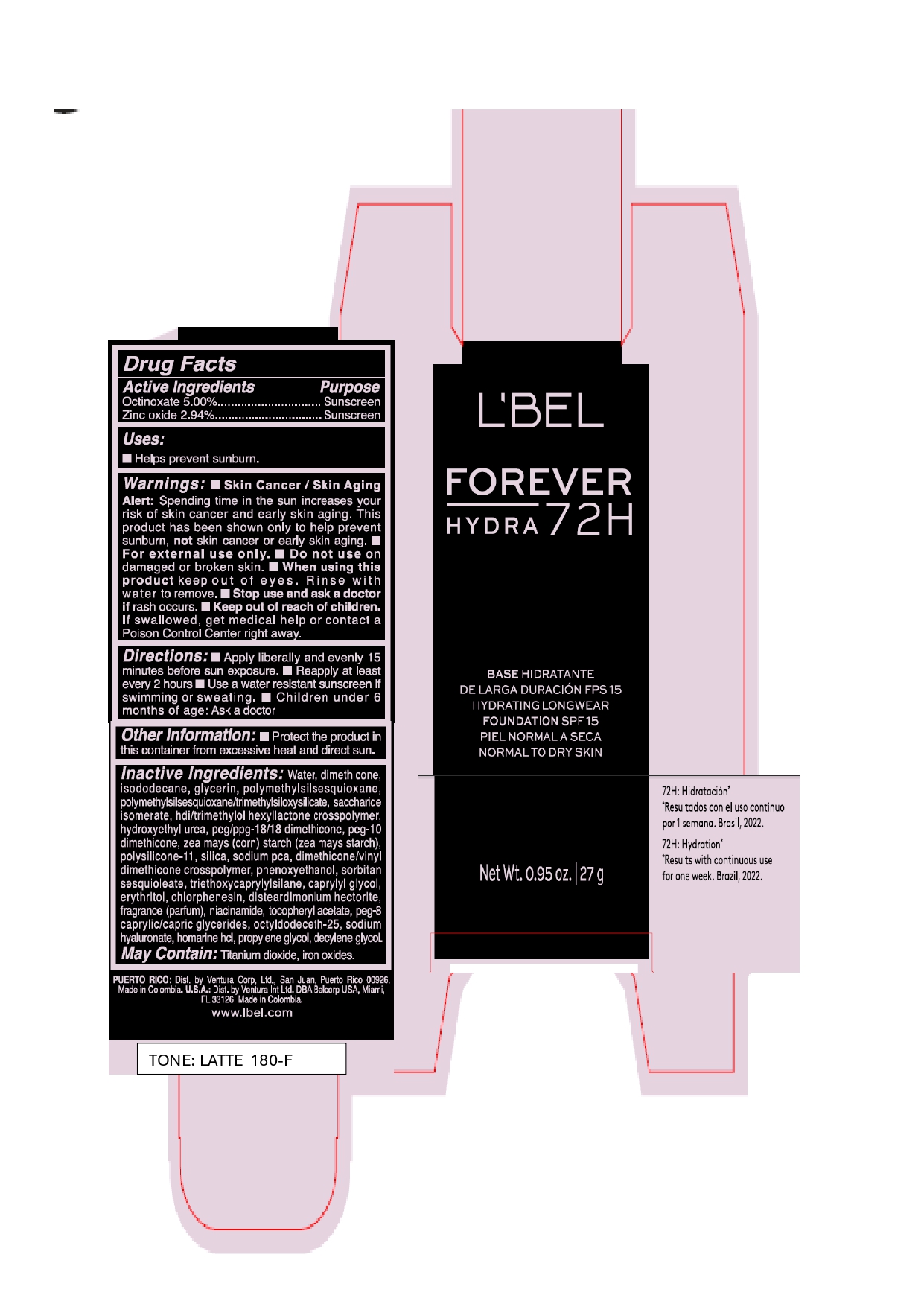 DRUG LABEL: LBEL FOREVER HYDRA BASE HIDRATANTE DE LARGA DURACION FPS 15 HYDRATING LONGWEAR FOUNDATION SPF 15 CAPUCCINO 310-C
NDC: 14141-345 | Form: EMULSION
Manufacturer: BEL STAR S A
Category: otc | Type: HUMAN OTC DRUG LABEL
Date: 20240710

ACTIVE INGREDIENTS: OCTINOXATE 50 mg/1 g; ZINC OXIDE 29.4 mg/1 g
INACTIVE INGREDIENTS: STARCH, CORN; PEG/PPG-18/18 DIMETHICONE; DIMETHICONE/VINYL DIMETHICONE CROSSPOLYMER (SOFT PARTICLE); SILICON DIOXIDE; GLYCERIN; PHENOXYETHANOL; DISTEARDIMONIUM HECTORITE; TITANIUM DIOXIDE; TRIETHOXYCAPRYLYLSILANE; CHLORPHENESIN; OCTYLDODECETH-25; POLYMETHYLSILSESQUIOXANE/TRIMETHYLSILOXYSILICATE; POLYMETHYLSILSESQUIOXANE (4.5 MICRONS); HYDROXYETHYL UREA; SACCHARIDE ISOMERATE; HEXAMETHYLENE DIISOCYANATE/TRIMETHYLOL HEXYLLACTONE CROSSPOLYMER; PEG-10 DIMETHICONE (600 CST); SODIUM PYRROLIDONE CARBOXYLATE; HOMARINE HYDROCHLORIDE; DECYLENE GLYCOL; ISODODECANE; PEG-8 CAPRYLIC/CAPRIC GLYCERIDES; PROPYLENE GLYCOL; FERRIC OXIDE RED; HYALURONATE SODIUM; FERRIC OXIDE YELLOW; FERROSOFERRIC OXIDE; DIMETHICONE; .ALPHA.-TOCOPHEROL ACETATE; CAPRYLYL GLYCOL; ERYTHRITOL; NIACINAMIDE; SORBITAN SESQUIOLEATE; WATER

L'BEL FOREVER HYDRA BASE HIDRATANTE DE LARGA DURACIÓN FPS 15 HYDRATING LONGWEAR FOUNDATION SPF 15

Active ingredients

Octinoxate 5.00%

Zinc oxide 2.94%

Purpose

Sunscreen

Uses

- Helps prevent sunburn.

Warnings

- Skin Cancer / Skin Aging Alert: Spending time in the sun increases your risk of skin cancer and early skin aging. This product has been shown only to help prevent sunburn, not skin cancer or early skin aging.
- For external use only.

Do not use

on damaged or broken skin.

When using this product

keep out of eyes. Rinse with water to remove.

Stop use and ask a doctor

if rash occurs.

Keep out of reach of children.

If swallowed, get medical help or contact a Poison Control Center right away.

Directions

- Apply liberally and evenly 15 minutes before sun exposure.
- Reapply at least every 2 hours
- Use a water resistant sunscreen if swimming or sweating
- Childrend under 6 months of age: Ask a doctor

Other information

- Protect the product in this container from excessive heat and direct sun.

Inactive ingredients

Water, dimethicone, isododecane, glycerin, polymethylsilsesquioxane, polymethylsilsesquioxane/trimethylsiloxysilicate, saccharide isomerate, hdi/trimethylol hexyllactone crosspolymer, hydroxyethyl urea, peg/ppg-18/18 dimethicone, peg-10 dimethicone, zea mays (corn) starch (zea mays starch), polysilicone-11, silica, sodium pca, dimethicone/vinyl dimethicone crosspolymer, phenoxyethanol, sorbitan sesquioleate, triethoxycaprylylsilane, caprylyl glycol, erythritol, chlorphenesin, disteardimonium hectorite, fragrance (parfum), niacinamide, tocopheryl acetate, peg-8 caprylic/capric glycerides, octyldodeceth-25, sodium hyaluronate, homarine hcl, propylene glycol, decylene glycol.

May Contain: Titanium dioxide, iron oxides.

Company Information

PUERTO RICO: Dist. by Ventura Corp, Ltd., San Juan, Puerto Rico 00926.

Made in Colombia. U.S.A.: Dist. by Ventura Int Ltd. DBA Belcorp USA, Miami, FL 33126. Made in Colombia.

www.lbel.com